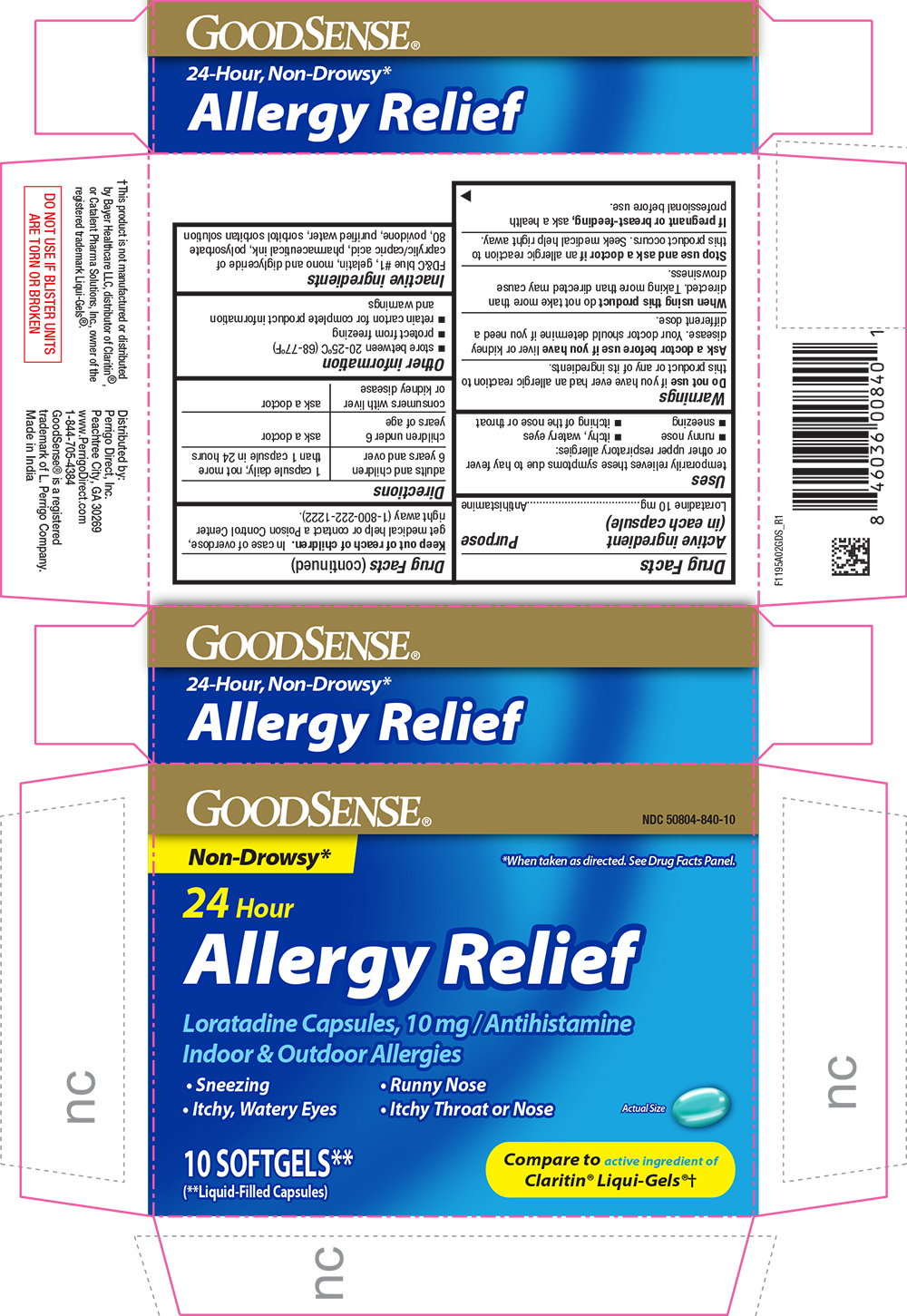 DRUG LABEL: Allergy Relief
NDC: 50804-840 | Form: CAPSULE, LIQUID FILLED
Manufacturer: GOODSENSE
Category: otc | Type: HUMAN OTC DRUG LABEL
Date: 20251209

ACTIVE INGREDIENTS: LORATADINE 10 mg/1 1
INACTIVE INGREDIENTS: FD&C BLUE NO. 1; GELATIN; CAPRIC ACID; POVIDONE K30; WATER; SORBITOL; POLYSORBATE 80; SORBITAN

GDS - 1195A - 2022-1118

Drug Facts

Active Ingredient (in each capsule)

Loratadine 10mg

Purpose

Antihistamine

Uses

temporarily relieves these symptoms due to hay fever or other upper respiratory allergies

• runny nose

• sneezing

• itchy, water eyes

• itching of the nose or throat

Warnings

Do not use if you have ever had an allergic reaction to this product or any of its ingredients.

Ask a doctor before use if you have liver or kidney disease. Your doctor should determine if you need a different dose.

When using this product do not take more than directed. Taking more than directed may cause drowsiness.

Stop use and ask a doctor if an allergic reaction to this product occurs. Seek medical help right away

PREGNANCY OR BREAST FEEDING

If pregnant or breast-feeding, ask a health professional before use.

Keep out of reach of children. In case of overdose, get medical help or contact a Poison Control Center right away (1-800-222-1222).

Directions

adults and children 6 years and over | 1 capsule daily; not more than 1 capsule in 24 hours
children under 6 years of age | ask a doctor
consumers with liver or kidney disease | ask a doctor

Other information

• Store between 20-25˚C (68-77˚F)

• protect from freezing

• retain carton for complete information and warnings

Inactive ingredients

FD&C Blue no. 1, gelatine, mono anddiglyceride of caprilic/capric acid, pharmaceutical ink, polysorbate 80,povidone, purified water, sorbitol, sorbitan solution.

Questions or Comments?

1-844-705-4384

PRINCIPAL DISPLAY PANEL

GOODSENSE®

NDC 50804-840-10

Non-Drowsy*

*When taken as directed. See Drug Facts Panel.

24 Hour

Allergy Relief

Loratadine Capsules, 10mg / Antihistamine

Indoor & Outdoor Allergies

• Sneezing •Runny Nose

• Itchy, Watery Eyes • Itchy Throat or Nose

10 SOFTGELS**

(**Liquid-Filled Capsules)

Compare to the active ingredient of Claritin® Liqui-Gels®